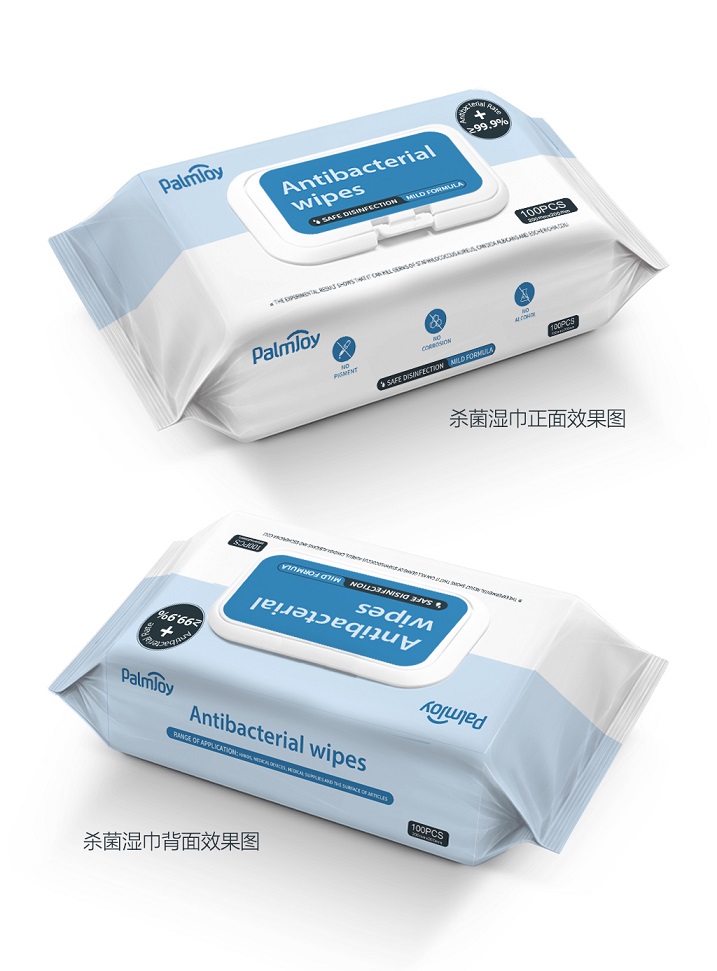 DRUG LABEL: Antibacterial Wipes
NDC: 75543-201 | Form: PATCH
Manufacturer: Fujian Yifa Healthcare Products Co., Ltd.
Category: otc | Type: HUMAN OTC DRUG LABEL
Date: 20200505

ACTIVE INGREDIENTS: BENZALKONIUM CHLORIDE 0.15 U/100 U; DIDECYLDIMONIUM CHLORIDE 0.2 U/100 U
INACTIVE INGREDIENTS: GLYCERIN; PHENOXYETHANOL; WATER; PROPYLENE GLYCOL

Yifa, Antibacterial Wipes, 2 AIs, *100

Active ingredient

Benzalkonium Chloride, 0.15% w/w;

Didecyldimonium Chloride, 0.2% w/w.

Inactive ingredient

Phenoxyethanol, Propylene Glycol, Glycerin, Water.

Purpose

Kill germs of staphylococcus aureus, candida albicans and escherichia coli.

When using

Antibacterial for hands, medical devices, medical supplies and the surface of articles.

Do not use

- on children less than 2 months of age
- on open skin wounds

Stop use

Stop to use immediately if having a negative impact on the objects and flush with water.

Keep out of reach of children

Indications & usage

Skin’s cleaning care, Article surface’s cleaning and maintenance.

Remove seal, pull out sheet and wipe skin or articles.

(For external use only)

Dosage & administration

Use it as needed, after following the usage instructions.

For external use only.

Warnings

- Discard immediately after use, and cover the lid in time.
- Follow the principle” One wipe to one article” to avoid cross-infection.
- Avoid contact with eyes. If contact occurs, immediately flush with water.
- External use Prohibit internal use.
- Be sure to wear gloves when having hand cut or be allergic to wipes.